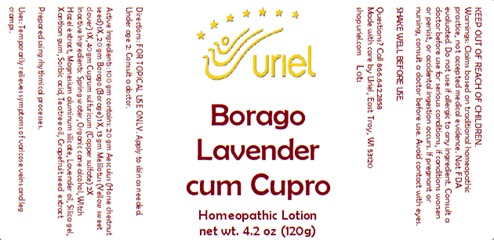 DRUG LABEL: Borago Lavender cum Cupro
NDC: 48951-2153 | Form: LOTION
Manufacturer: Uriel Pharmacy, Inc.
Category: homeopathic | Type: HUMAN OTC DRUG LABEL
Date: 20240905

ACTIVE INGREDIENTS: MELILOTUS INDICUS SEED 1 [hp_X]/1 g; CUPRIC SULFATE 2 [hp_X]/1 g; BORAGE 1 [hp_X]/1 g; HORSE CHESTNUT 1 [hp_X]/1 g
INACTIVE INGREDIENTS: LAVENDER OIL; TEA TREE OIL; XANTHAN GUM; HAMAMELIS VIRGINIANA TOP WATER; WATER; MAGNESIUM ALUMINUM SILICATE; SILICON DIOXIDE; SORBIC ACID; CITRUS PARADISI SEED

Borago Lavender cum Cupro

INDICATIONS AND USAGE

Directions: FOR TOPICAL USE ONLY.

DOSAGE AND ADMINISTRATION

Apply to skin as needed. Under age 2: Consult a doctor.

ACTIVE INGREDIENT

Active Ingredients: 100gm contains: 20gm Aesculus (Horse chestnut seed) 1X, 20gm Borago (Borage) 1X, 13gm Melilotus (Yellow sweet clover) 1X, 40gm Cuprum sulfuricum (Copper sulfate) 2X

INACTIVE INGREDIENT

Inactive Ingredients: Spring water, Organic cane alcohol, Witch hazel extract, Magnesium aluminum silicate, Lavender oil, Silica gel, Xanthan gum, Sorbic acid, Tea tree oil,Grapefruit seed extract

Prepared using rhythmical processes.

PURPOSE

Uses: Temporarily relieves symptoms of varicose veins and leg cramps.

KEEP OUT OF REACH OF CHILDREN.

Warnings:
Claims based on traditional homeopathic practice, not accepted medical evidence. Not FDA evaluated.
Do not use if allergic to any ingredient. Consult a doctor before use for serious conditions, if conditions worsen or persist,
or accidental ingestion occurs. If pregnant or nursing, consult a doctor before use. Avoid contact with eyes.

SHAKE WELL BEFORE USE.

Questions? Call 866.642.2858
Made with care by Uriel, East Troy, WI 53120
shopuriel.com Lot: